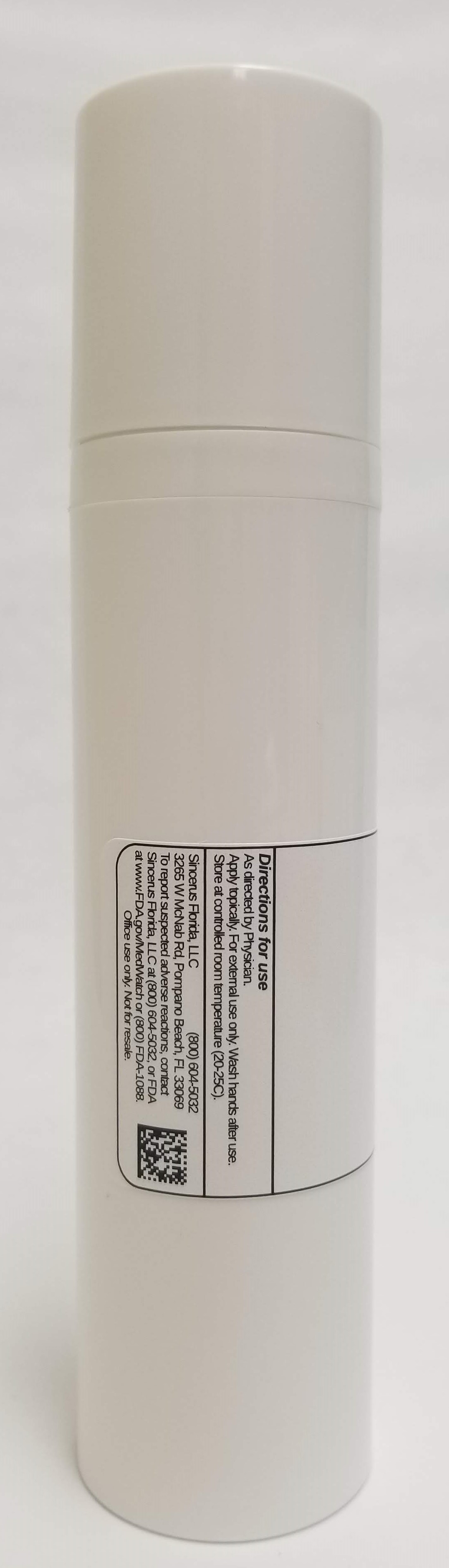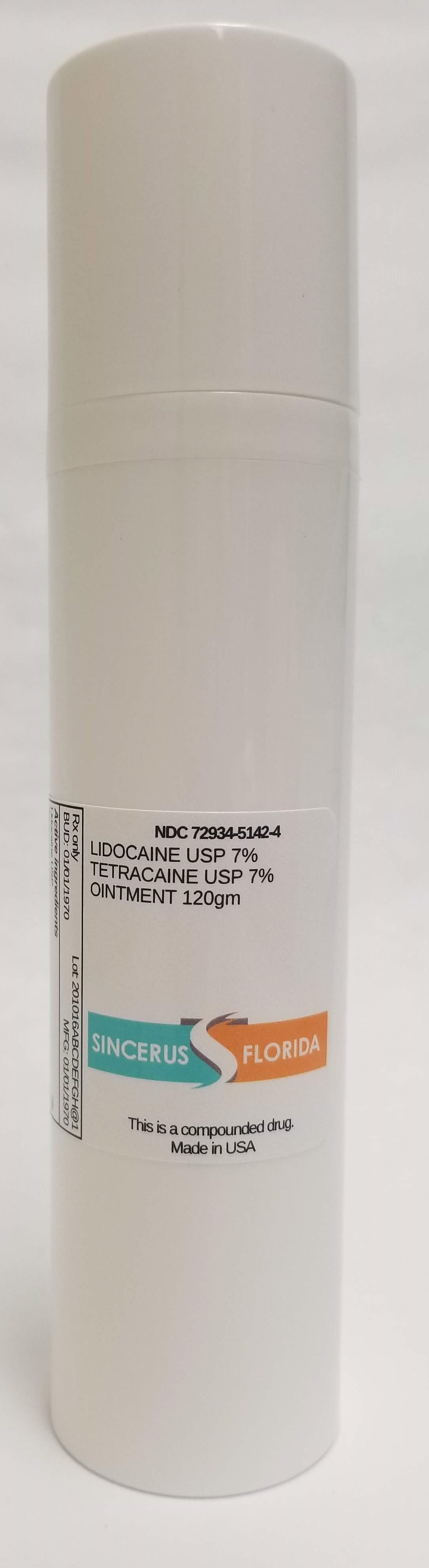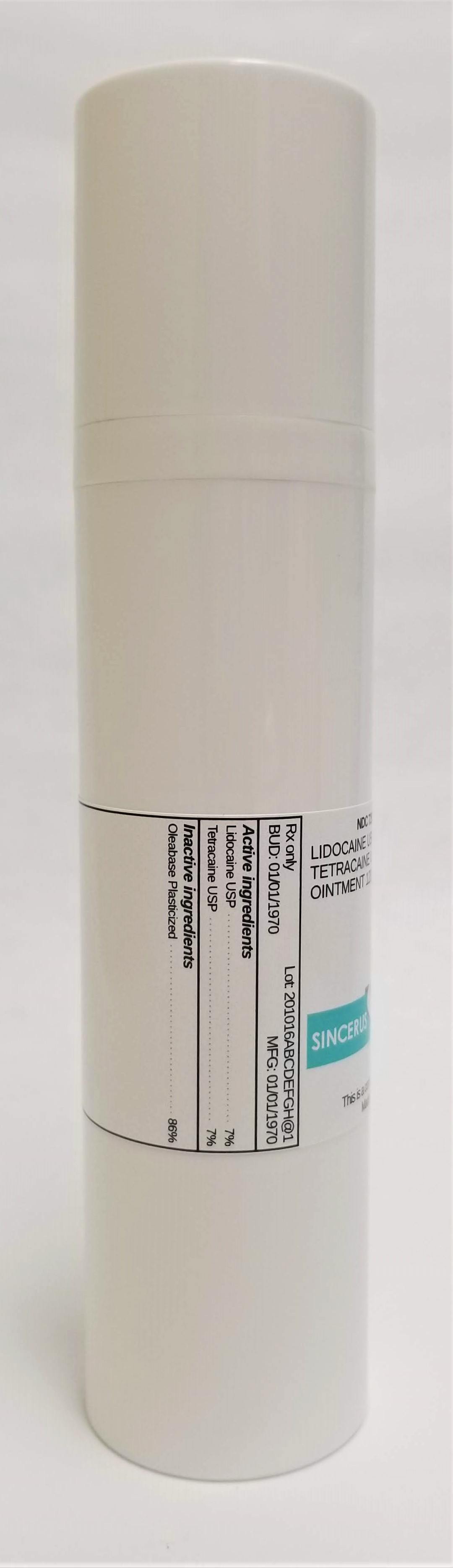 DRUG LABEL: LIDOCAINE 7% / TETRACAINE 7%
NDC: 72934-5142 | Form: OINTMENT
Manufacturer: Sincerus Florida, LLC
Category: prescription | Type: HUMAN PRESCRIPTION DRUG LABEL
Date: 20190517

ACTIVE INGREDIENTS: LIDOCAINE 7 g/100 g; TETRACAINE 7 g/100 g

LIDOCAINE 7% / TETRACAINE 7%